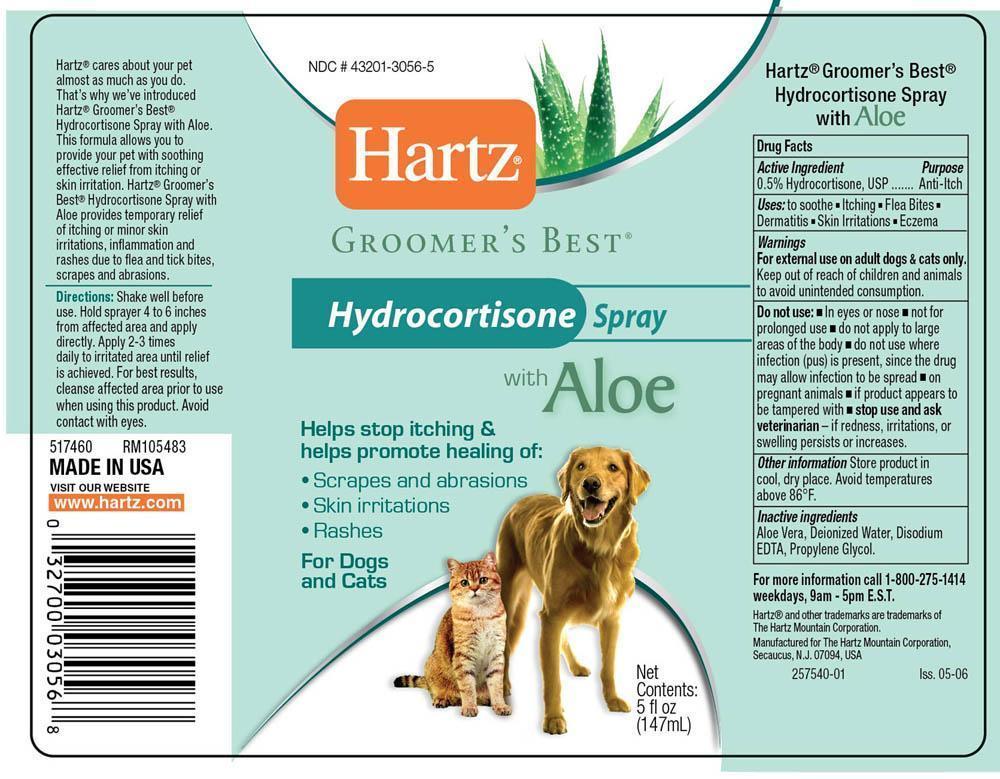 DRUG LABEL: Hartz
NDC: 43201-3056 | Form: SPRAY
Manufacturer: The Hartz Mountain Corporation
Category: animal | Type: OTC ANIMAL DRUG LABEL
Date: 20130422

ACTIVE INGREDIENTS: HYDROCORTISONE 0.5 g/100 mL
INACTIVE INGREDIENTS: ALOE VERA LEAF; WATER; EDETATE DISODIUM; PROPYLENE GLYCOL

Drug Facts

Active Ingredient

0.5% Hydrocortisone, USP

Purpose

Anti-itch

INDICATIONS AND USAGE

Uses to soothe ▪ Itching ▪Flea bites ▪Dermatitis ▪Skin Irratations ▪Eczema

Warnings

For external use on adult dogs and cats only.

Keep out of the reach of children and animnals to avoid unintended consumption.

Do not use ▪In eyes or nose ▪not for prolonged use ▪do not apply to large areas of the body ▪do not use where infection (pus) is present, since the drug may allow the infection to be spread ▪on pregnant animals ▪ if product appears to be tasmpered with

stop use and ask a veterinarian if redness, irritations, or swelling persists or increases

DOSAGE AND ADMINISTRATION

Directions: Shake well before use. Hold sprayer 4 to 6 inches from affected area and apply directly. Apply 2-3 times daily to irritated area until relief is achieved. For best results, cleanse affected area prior to use when using this product. Avoid contact with eyes

Other informationStore product in cool, dry place. Avoid temperatures above 86F

Inactive Ingredients

Aloe Vera Gel, Deionized Water, Disodium EDTA, Propylene Glycol